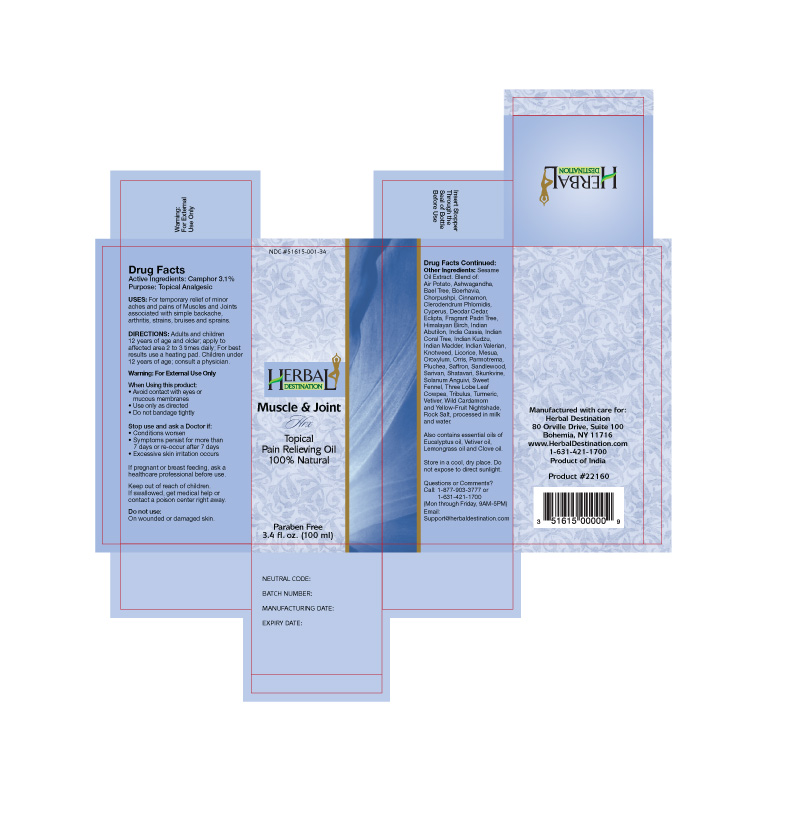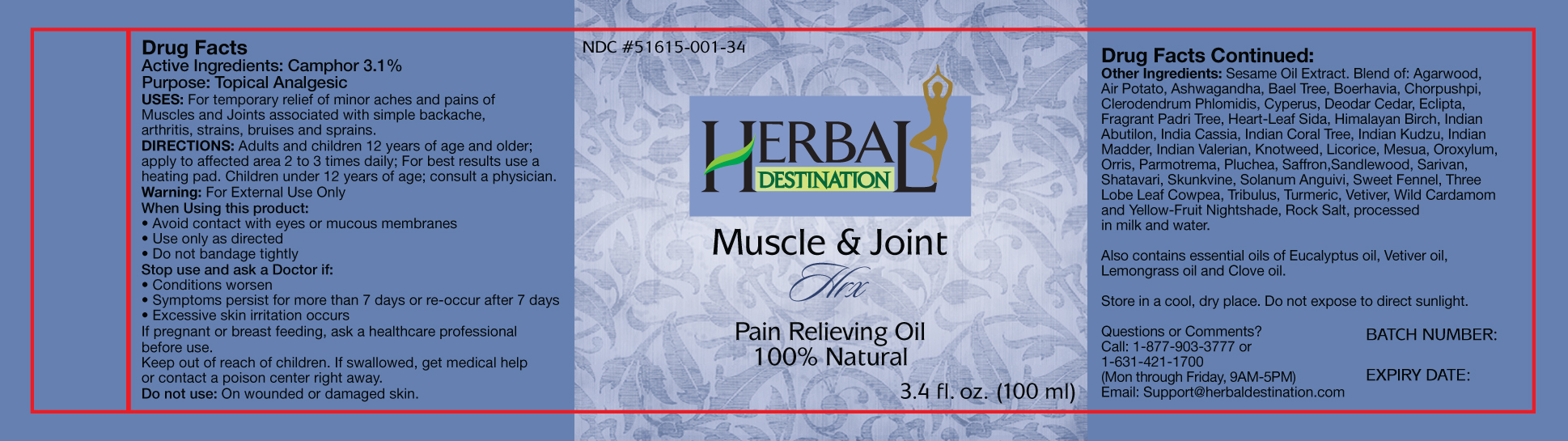 DRUG LABEL: Muscle and Joint HRX
NDC: 51615-001 | Form: OIL
Manufacturer: Eximus Connections d/b/a Herbal Destination
Category: otc | Type: HUMAN OTC DRUG LABEL
Date: 20120911

ACTIVE INGREDIENTS: CAMPHOR (NATURAL) 3 mL/100 mL
INACTIVE INGREDIENTS: SESAME OIL; CYPERUS ROTUNDUS ROOT; LICORICE; PERSICARIA TINCTORIA LEAF; SAFFRON; FENNEL; TURMERIC; EUCALYPTUS OIL; CLOVE OIL

Active Ingredients:

Camphor 3.1%

Purpose:

Topical Analgesic

Uses:

For temporary relief of minor aches and pains of Muscles and Joints associated with simple backache, arthritis, strains, bruises and sprains.

Directions:

Adults and children 12 years of age and older: apply to affected area 2 to 3 times daily; For best results, use a heating pad. Children under 12 years of age: consult a physician.

Warnings:

For External Use Only

When Using this product:

- Avoid contact with eyes or mucous membranes
- Use only as directed
- Do not bandage tightly

Stop use and ask a Doctor if:

- Conditions worsen
- Symptoms persist for more than 7 days or re-occur after 7 days
- Excessive skin irritation occurs

PREGNANCY OR BREAST FEEDING

If pregnant or breast feeding, ask a health care professional before use.

Keep out of reach of children. If swallowed, get medical help or contact a poison center right away.

Do not use:

On wounded or damaged skin

Other Ingredients:

Sesame Oil Extract, Blend of: Agarwood, Air Potato, Ashwagandha, Bael Tree, Boerhavia, Chorpushpi, Clerodendrum Phlomidis, Cyperus, Deodar Cedar, Eclipta, Fragrant Padri Tree, Heart-Leaf Side, Himalayan Birch, Indian Abutilon, India Cassia, Indian Coral Tree, Indian Kudzu, Indian Madder, Indian Valerian, Knotweed, Licorice, Mesua, Oroxylum, Orris, Parmotrema, Pluchea, Saffron, Sandlewood, Sarivan, Shatavari, Skunkvine, Solanum Anguivi, Sweet Fennel, Three Lobe Leaf Cowpea, Tribulus, Turmeric, Vetiver, Wild Cardamom and Yellow-Fruit Nightshade, Rock salt, processed in milk and water

Also contains essential oils of: Eucalyptus oil, Vetiver oil, Lemongrass oil and Clove Oil

STORAGE AND HANDLING

Store in a cool, dry place. Do not expose to direct sunlight.

Questions or Comments?

Call: 1-877-90303777 or 1-631-421-1700 (Mon Through Friday, 9AM-5PM)

Email: Support@herbaldestination.com

DESCRIPTION

Manufactured with care for:
Herbal Destination
80 Orville Drive, Suite 100
Bohemia, NY 11716
www.HerbalDestination.com
1-631-421-1700
Product of India

PACKAGE LABEL

Herbal Destination

Muscle and Joint HRX

Topical

Pain Relieving OIl

100% Natural

Paraben Free
3.4 fl oz (100 ml)